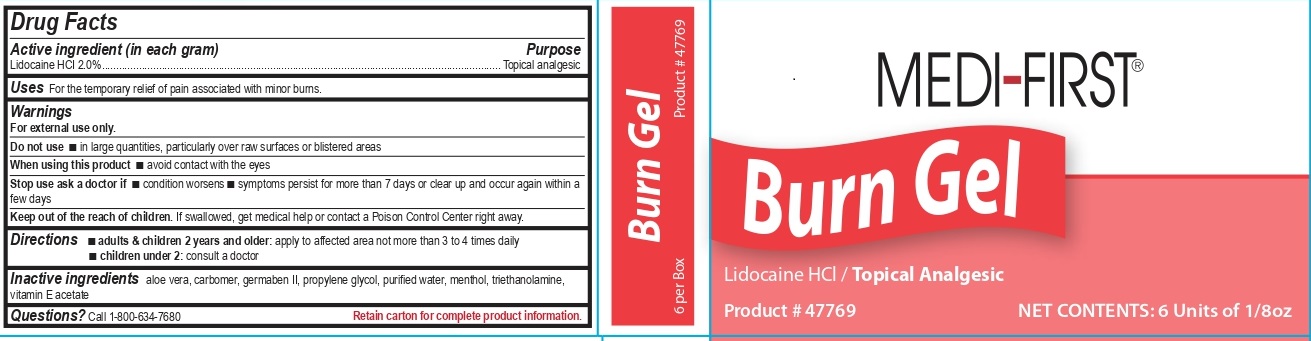 DRUG LABEL: Medi-First Burn
NDC: 47682-477 | Form: GEL
Manufacturer: Unifirst First Aid Corporation
Category: otc | Type: HUMAN OTC DRUG LABEL
Date: 20250909

ACTIVE INGREDIENTS: LIDOCAINE HYDROCHLORIDE 20 mg/1 g
INACTIVE INGREDIENTS: DIAZOLIDINYL UREA; PROPYLENE GLYCOL; WATER; ALOE VERA LEAF; MENTHOL; TROLAMINE; .ALPHA.-TOCOPHEROL ACETATE; CARBOMER INTERPOLYMER TYPE A (ALLYL SUCROSE CROSSLINKED); PROPYLPARABEN; METHYLPARABEN

Medi-First Burn Gel Drug Facts

Drug Facts

Active ingredient (in each gram)

Lidocaine HCI 2.0%

Purpose

Topical analgesic

Uses

For the temporary relief of pain associated with minor burns.

Warnings

For external use only.

Do not use

- in large quantities, particularly over raw or blistered areas

When using this product

- avoid contact with the eyes

Stop use ask a doctor if

- condition worsens
- symptoms persist for more than 7 days or clears up and occurs again within a few days

Keep out of the reach of children.

If swallowed, get medical help or contact a Poison Control Center right away.

Directions

- adults & children 2 years and older: apply to affected area not more than 3 to 4 times daily
- children under 2: consult a doctor

Inactive ingredients

aloe vera, carbomer, germaben II, propylene glycol, purified water, menthol, triethanolamine, vitamin E acetate

Questions?

Call 1-800-634-7680

Mfg. for Medique Products, 17080 Alico Commerce Ct., Ste 1, Fort Myers, FL 33967

Medi-First Burn Gel Label

Medi-First ®

Burn Gel

Lidocaine HCl / Topical Analgesic

Product # 47769

NET CONTENTS: 6 Units of 1/8 oz